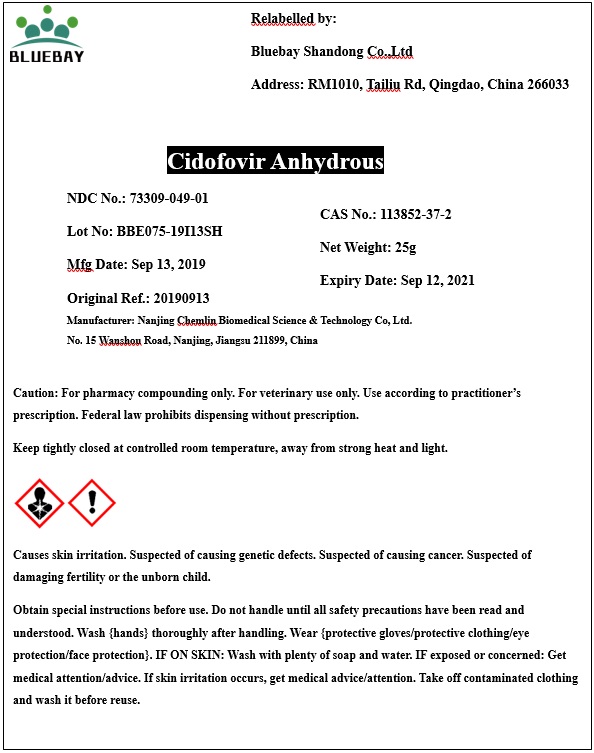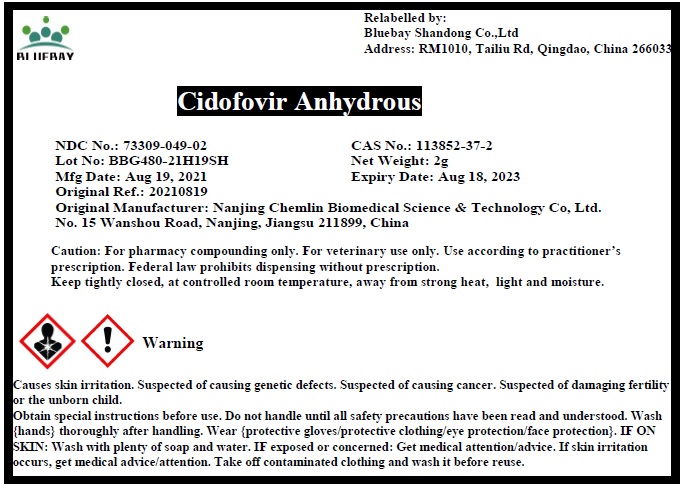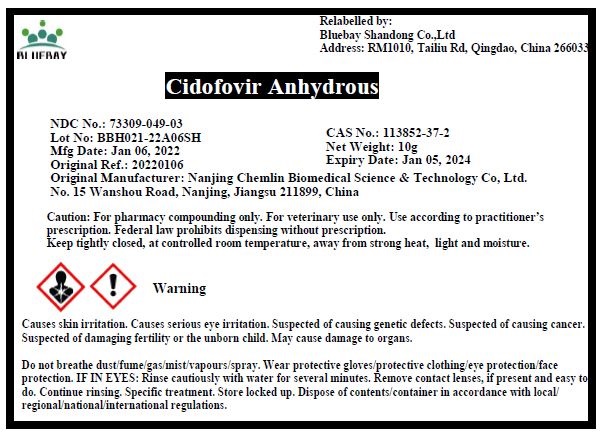 DRUG LABEL: Cidofovir Anhydrous
NDC: 73309-049 | Form: POWDER
Manufacturer: BLUEBAY SHANDONG CO.,LTD
Category: other | Type: BULK INGREDIENT
Date: 20220114

ACTIVE INGREDIENTS: CIDOFOVIR ANHYDROUS 1 g/1 g

Cidofovir Anhydrous